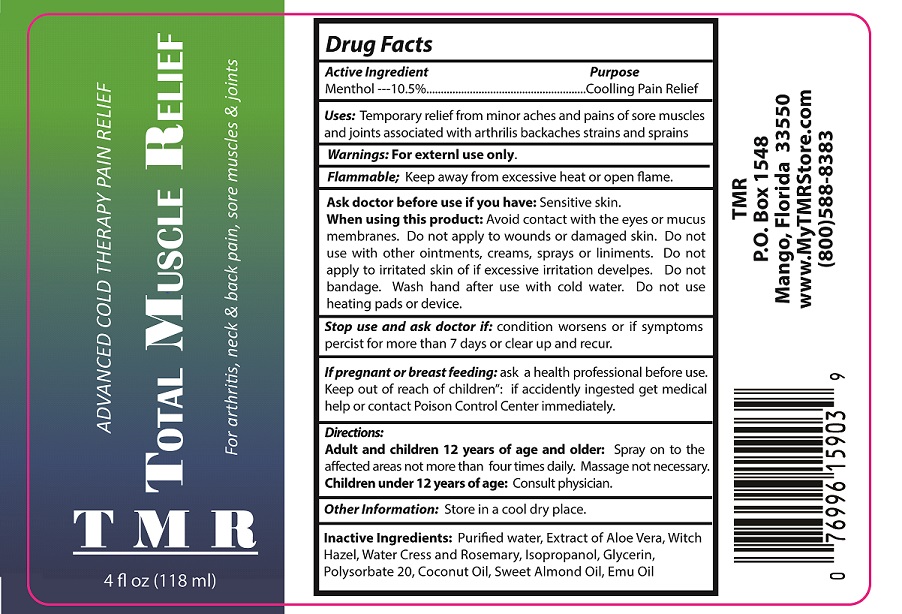 DRUG LABEL: TOTAL MUSCLE RELIEF
NDC: 50130-109 | Form: SPRAY
Manufacturer: Electrostim Medical Services Inc. d/b/a EMSI
Category: otc | Type: HUMAN OTC DRUG LABEL
Date: 20190216

ACTIVE INGREDIENTS: MENTHOL 10.5 g/100 mL
INACTIVE INGREDIENTS: WATER; ALOE VERA LEAF; WITCH HAZEL; WATERCRESS; ROSEMARY; ISOPROPYL ALCOHOL; GLYCERIN; POLYSORBATE 20; COCONUT OIL; ALMOND OIL; EMU OIL

Active Ingredient

Menthol ---10.5%

Purpose

Cooling Pain Relief

USES

Temporary relief from minor aches and pains of sore muscles and joints associated with arthrilis backaches strains and sprains

WARNINGS

For external use only.
Flammable; Keep away from excessive heat or open-flame.
Ask doctor before use if you have: Sensitive skin.
When using this product: Avoid contact with the eyes or mucus membranes. Do not apply to wounds or damaged skin. Do not use with other ointments, creams, sprays or liniments. Do not apply to irritated skin of if excessive irritation develops. Do not bandage. Wash hand after use with cold water. Do not use heating pads or device. Store in a cool dry place. Stop use and ask doctor if: condition worsens or if symptoms persist for more than 7 days or clear up and recur.
If pregnant or breast feeding: ask a health professional before use.

Keep out of reach of children: if accidently ingested get medical help or contact Poison Control Center immediately

DIRECTIONS

Adult and children 12 years of age and older: Spray on to the affected areas not more than four times daily. Massage not necessary.
Children under 12 years of age: Consult physician.

Inactive ingredients

Purified water, Extract of Aloe Vera, Witch Hazel, Water Cress and Rosemary, Isopropanol, Glycerin, Polysorbate 20, Coconut Oil, Sweet Almond Oil, Emu Oil